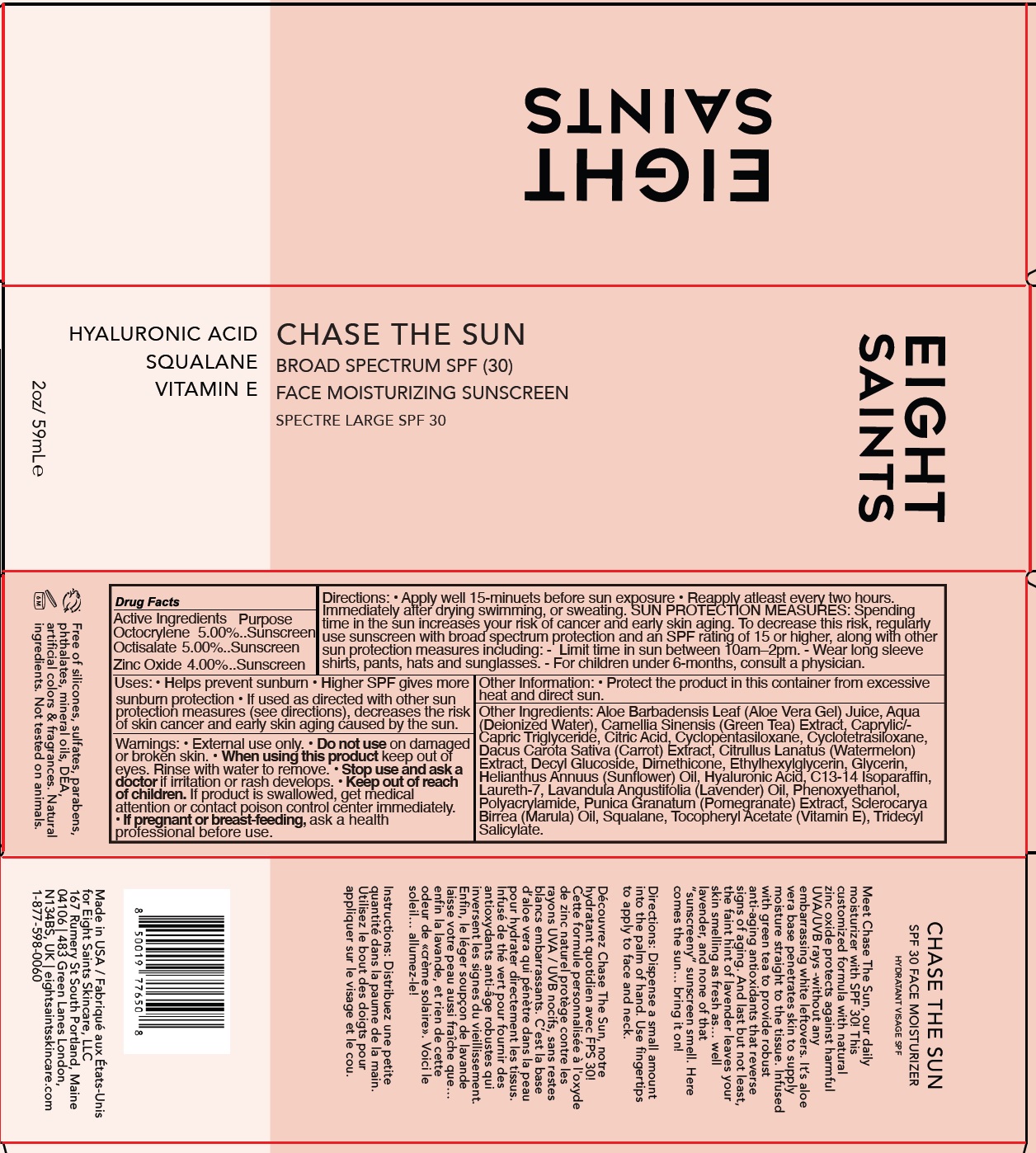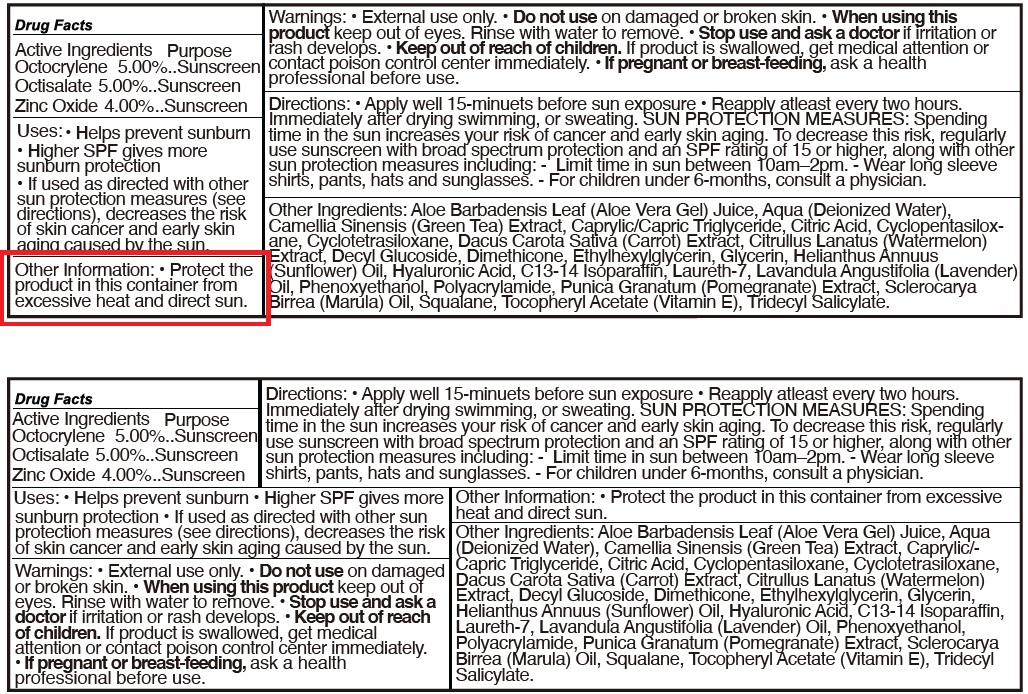 DRUG LABEL: EIGHT SAINTS Chase The Sun SPF-30
NDC: 82247-384 | Form: CREAM
Manufacturer: BRICKELL BRANDS LLC
Category: otc | Type: HUMAN OTC DRUG LABEL
Date: 20231111

ACTIVE INGREDIENTS: OCTOCRYLENE 50 mg/1 mL; OCTISALATE 50 mg/1 mL; ZINC OXIDE 40 mg/1 mL
INACTIVE INGREDIENTS: ALOE VERA LEAF; WATER; GREEN TEA LEAF; MEDIUM-CHAIN TRIGLYCERIDES; CITRIC ACID MONOHYDRATE; CYCLOMETHICONE 5; CYCLOMETHICONE 4; CARROT; WATERMELON; DECYL GLUCOSIDE; DIMETHICONE; ETHYLHEXYLGLYCERIN; GLYCERIN; HELIANTHUS ANNUUS FLOWERING TOP; HYALURONIC ACID; C13-14 ISOPARAFFIN; LAURETH-7; LAVENDER OIL; PHENOXYETHANOL; PUNICA GRANATUM ROOT BARK; SQUALANE; .ALPHA.-TOCOPHEROL ACETATE; TRIDECYL SALICYLATE

EIGHT SAINTS Chase The Sun SPF-30

Active Ingredients

Octocrylene 5.00%

Octisalate 5.00%

Zinc Oxide 4.00%

Purpose

Sunscreen

Uses:

• Helps prevent sunburn • Higher SPF gives more sunburn protection • If used as directed with other sun protection measures (see directions), decreases the risk of skin cancer and early skin aging caused by the sun.

Warnings:

• External use only.

Do not use

• on damaged or broken skin.

When using this product

• keep out of eyes. Rinse with water to remove.

Stop use and ask a doctor

• if irritation or rash develops.

Keep out of reach of children.

• If product is swallowed, get medical attention or contact poison control center immediately.

If pregnant or breast-feeding,

• ask a health professional before use.

Directions:

• Apply well 15-minuets before sun exposure • Reapply atleast every two hours. Immediately after drying swimming, or sweating. Spending time in the sun increases your risk of cancer and early skin aging. To decrease this risk, regularly use sunscreen with broad spectrum protection and an SPF rating of 15 or higher, along with other sun protection measures including: - Limit time in sun between 10am–2pm. - Wear long sleeve shirts, pants, hats and sunglasses. - For children under 6-months, consult a physician. SUN PROTECTION MEASURES:

Other Information:

• Protect the product in this container from excessive heat and direct sun.

Other Ingredients:

Aloe Barbadensis Leaf (Aloe Vera Gel) Juice, Aqua (Deionized Water), Camellia Sinensis (Green Tea) Extract, Caprylic/- Capric Triglyceride, Citric Acid, Cyclopentasiloxane, Cyclotetrasiloxane, Dacus Carota Sativa (Carrot) Extract, Citrullus Lanatus (Watermelon) Extract, Decyl Glucoside, Dimethicone, Ethylhexylglycerin, Glycerin, Helianthus Annuus (Sunflower) Oil, Hyaluronic Acid, C13-14 Isoparaffin, Laureth-7, Lavandula Angustifolia (Lavender) Oil, Phenoxyethanol, Polyacrylamide, Punica Granatum (Pomegranate) Extract, Sclerocarya Birrea (Marula) Oil, Squalane, Tocopheryl Acetate (Vitamin E), Tridecyl Salicylate.